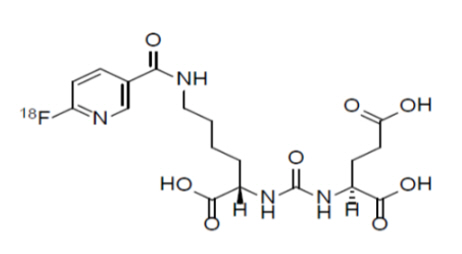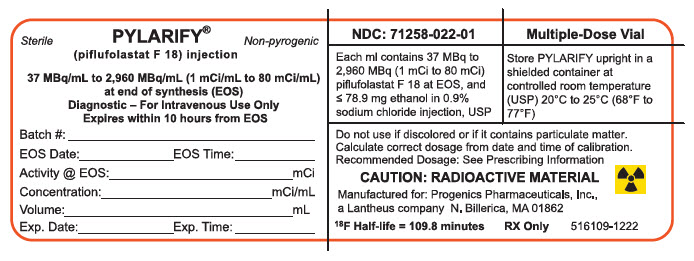 DRUG LABEL: PYLARIFY
NDC: 71258-022 | Form: INJECTION
Manufacturer: Progenics Pharmaceuticals, Inc.
Category: prescription | Type: HUMAN PRESCRIPTION DRUG LABEL
Date: 20250304

ACTIVE INGREDIENTS: PIFLUFOLASTAT F-18 80 mCi/1 mL
INACTIVE INGREDIENTS: ALCOHOL; ISOTONIC SODIUM CHLORIDE SOLUTION

HIGHLIGHTS OF PRESCRIBING INFORMATION

These highlights do not include all the information needed to use PYLARIFY®safely and effectively. See full prescribing information for PYLARIFY.
PYLARIFY®(piflufolastat F 18) injection, for intravenous use
Initial U.S. Approval: 2021

1 INDICATIONS AND USAGE

PYLARIFY is a radioactive diagnostic agent indicated for positron emission tomography (PET) of prostate-specific membrane antigen (PSMA) positive lesions in men with prostate cancer:

- with suspected metastasis who are candidates for initial definitive therapy.
- with suspected recurrence based on elevated serum prostate-specific antigen (PSA) level. (1)

2 DOSAGE AND ADMINISTRATION

- Recommended dose is 333 MBq (9 mCi) with an acceptable range of 296 MBq to 370 MBq (8 mCi to 10 mCi), administered as a bolus intravenous injection. (2.2)
- Initiate imaging approximately 60 minutes after PYLARIFY administration. The patient should void immediately prior to initiation of imaging. Image acquisition should start from mid-thigh and proceed to the skull vertex. (2.3, 2.4)
- See full prescribing information for additional preparation, handling, administration, imaging, and radiation dosimetry information. (2)

3 DOSAGE FORMS AND STRENGTHS

Injection: clear, colorless solution in a multiple-dose vial containing 37 MBq/mL to 2,960 MBq/mL (1 mCi/mL to 80 mCi/mL) of piflufolastat F 18 at calibration date and time. (3)

4 CONTRAINDICATIONS

None. (4)

5 WARNINGS AND PRECAUTIONS

- Risk of Image Misinterpretation: PYLARIFY uptake can be seen in a variety of tumor types as well as in non-malignant processes and normal tissues. Image interpretation errors can occur with PYLARIFY imaging. (5.1)
- Hypersensitivity Reactions: Monitor patients for hypersensitivity reactions, particularly patients with a history of allergy to other drugs and foods. (5.2)
- Radiation Risk: Ensure safe drug handling to protect patients and health care workers from unintentional radiation exposure. (5.3)

6 ADVERSE REACTIONS

The most common reported adverse reactions are headache, dysgeusia, and fatigue. (6.1)

To report SUSPECTED ADVERSE REACTIONS, contact Progenics Pharmaceuticals, Inc. at 1-800-362-2668 or FDA at 1-800-FDA-1088 or www.fda.gov/medwatch.

FULL PRESCRIBING INFORMATION

1 INDICATIONS AND USAGE

PYLARIFY is indicated for positron emission tomography (PET) of prostate-specific membrane antigen (PSMA) positive lesions in men with prostate cancer:

- with suspected metastasis who are candidates for initial definitive therapy.
- with suspected recurrence based on elevated serum prostate-specific antigen (PSA) level.

2 DOSAGE AND ADMINISTRATION

2.1 Radiation Safety – Drug Handling

PYLARIFY is a radioactive drug. Only authorized persons qualified by training and experience should receive, use, and administer PYLARIFY. Handle PYLARIFY with appropriate safety measures to minimize radiation exposure during administration [see Warnings and Precautions (5.3)] . Use waterproof gloves and effective radiation shielding, including syringe shields, when preparing and handling PYLARIFY.

2.2 Recommended Dosage and Administration Instructions

Recommended Dose

The recommended amount of radioactivity to be administered for PET imaging is 333 MBq (9 mCi) with an acceptable range of 296 MBq to 370 MBq (8 mCi to 10 mCi) administered as a single bolus intravenous injection.

Preparation and Administration

- Use aseptic technique and radiation shielding when preparing and administering PYLARIFY.
- Visually inspect the radiopharmaceutical solution. Do not use if it contains particulate matter or if it is discolored (PYLARIFY is a clear, colorless solution).
- Calculate the necessary volume to administer based on calibration time and required dose. PYLARIFY may be diluted with 0.9% Sodium Chloride Injection, USP.
- Assay the dose in a suitable dose calibrator prior to administration.

Post Administration Instructions

- Follow the PYLARIFY injection with an intravenous flush of 0.9% Sodium Chloride Injection USP.
- Dispose of any unused PYLARIFY in compliance with applicable regulations.

2.3 Patient Preparation

Instruct patients to drink water to ensure adequate hydration prior to administration of PYLARIFY and to continue drinking and voiding frequently for the first few hours following administration to reduce radiation exposure [see Warnings and Precautions (5.3)] .

2.4 Image Acquisition

The recommended start time for image acquisition is 60 minutes after PYLARIFY injection. Starting image acquisition more than 90 minutes after injection may adversely impact imaging performance. Patients should void immediately prior to image acquisition. Position the patient supine with arms above the head. Image acquisition should start from mid-thigh and proceed to the skull vertex. Scan duration is 12 minutes to 40 minutes depending on the number of bed positions (typically 6 to 8) and acquisition time per bed position (typically 2 minutes to 5 minutes).

2.5 Image Display and Interpretation

PYLARIFY binds to prostate-specific membrane antigen (PSMA). Based on the intensity of the signals, PET images obtained using PYLARIFY indicate the presence of PSMA in tissues. Lesions should be considered suspicious if uptake is greater than physiologic uptake in that tissue or greater than adjacent background if no physiologic uptake is expected. Tumors that do not express PSMA will not be visualized. Increased uptake in tumors is not specific for prostate cancer [ see Warnings and Precautions (5.1)].

2.6 Radiation Dosimetry

Radiation absorbed dose estimates are shown in Table 1 for organs and tissues of adult male patients from intravenous administration of PYLARIFY. The radiation effective dose resulting from administration of 370 MBq (10 mCi) of PYLARIFY to an adult weighing 70 kg is estimated to be 4.3 mSv. The radiation doses for this administered dose to the critical organs, which are the kidneys, liver, and spleen, are 45.5 mGy, 13.7 mGy, and 10 mGy respectively. When PET/CT is performed, exposure to radiation will increase by an amount dependent on the settings used in the CT acquisition.

Table 1. Estimated Radiation Absorbed Doses in Organs/Tissues in Adults who Received PYLARIFY
Organ/Tissue | Mean Absorbed dose per Unit Administered Activity (mGy/MBq)
 | Mean | Standard Deviation
Adrenal glands | 0.0131 | 0.0013
Brain | 0.0021 | 0.0003
Breasts | 0.0058 | 0.0007
Gallbladder wall | 0.0141 | 0.0012
Lower large intestine wall | 0.0073 | 0.001
Small intestine | 0.0089 | 0.0009
Stomach wall | 0.0092 | 0.0008
Upper large intestine wall | 0.0091 | 0.0009
Heart wall | 0.0171 | 0.0022
Kidneys | 0.123 | 0.0434
Liver | 0.037 | 0.0058
Lungs | 0.0102 | 0.0016
Muscle | 0.0069 | 0.0008
Pancreas | 0.0124 | 0.0011
Red bone marrow | 0.0071 | 0.0007
Osteogenic cells | 0.0099 | 0.0012
Skin | 0.0052 | 0.0006
Spleen | 0.0271 | 0.0115
Testes | 0.0059 | 0.0008
Thymus gland | 0.007 | 0.0008
Thyroid | 0.0062 | 0.0009
Urinary bladder wall | 0.0072 | 0.001
Effective dose | 0.0116 (mSv/MBq) | 0.0022 (mSv/MBq)

3 DOSAGE FORMS AND STRENGTHS

Injection: clear, colorless solution in a multiple-dose vial containing 37 MBq/mL to 2,960 MBq/mL (1 mCi/mL to 80 mCi/mL) of piflufolastat F 18 at calibration date and time.

4 CONTRAINDICATIONS

None.

5 WARNINGS AND PRECAUTIONS

5.1 Risk of Image Misinterpretation

Imaging interpretation errors can occur with PYLARIFY imaging. A negative image does not rule out the presence of prostate cancer and a positive image does not confirm the presence of prostate cancer. The performance of PYLARIFY for imaging of patients with biochemical evidence of recurrence of prostate cancer seems to be affected by serum PSA levels [ see Clinical Studies (14)]. The performance of PYLARIFY for imaging of metastatic pelvic lymph nodes prior to initial definitive therapy seems to be affected by risk factors such as Gleason score and tumor stage [ see Clinical Studies (14)]. PYLARIFY uptake is not specific for prostate cancer and may occur with other types of cancer as well as non-malignant processes and in normal tissues. Clinical correlation, which may include histopathological evaluation of the suspected prostate cancer site, is recommended.

5.2 Hypersensitivity Reactions

Monitor patients for hypersensitivity reactions, particularly patients with a history of allergy to other drugs and foods. Reactions may not be immediate. Always have trained staff and resuscitation equipment available.

5.3 Radiation Risks

Diagnostic radiopharmaceuticals, including PYLARIFY, expose patients to radiation [see Dosage and Administration (2.6)] . Radiation exposure is associated with a dose-dependent increased risk of cancer. Ensure safe handling and preparation procedures to protect patients and health care workers from unintentional radiation exposure. Advise patients to hydrate before and after administration and to void frequently after administration [see Dosage and Administration (2.3)] .

6 ADVERSE REACTIONS

6.1 Clinical Trials Experience

Because clinical trials are conducted under widely varying conditions, adverse reaction rates observed in the clinical trials of a drug cannot be directly compared to rates in the clinical trials of another drug and may not reflect the rates observed in practice.

The safety of PYLARIFY was evaluated in 593 patients, each receiving one dose of PYLARIFY. The average injected activity was 340 ± 26 MBq (9.2 ± 0.7 mCi).

The adverse reactions reported in >0.5% of patients within the studies are shown in Table 2. In addition, a hypersensitivity reaction was reported in one patient (0.2%) with a history of allergic reaction.

Table 2. Adverse Reactions with a Frequency >0.5% in Patients Who Received PYLARIFY (n = 593)
Adverse Reaction | n (%)
Headache | 13 (2%)
Dysgeusia | 10 (2%)
Fatigue | 7 (1%)

7 DRUG INTERACTIONS

Androgen deprivation therapy and other therapies targeting the androgen pathway

Androgen deprivation therapy (ADT) and other therapies targeting the androgen pathway, such as androgen receptor antagonists, may result in changes in uptake of PYLARIFY in prostate cancer. The effect of these therapies on performance of PYLARIFY PET has not been established.

8 USE IN SPECIFIC POPULATIONS

8.1 Pregnancy

Risk Summary

PYLARIFY is not indicated for use in females. There is no information on the risk of adverse developmental outcomes in pregnant women or animals with the use of piflufolastat F 18. All radiopharmaceuticals, including PYLARIFY, have the potential to cause fetal harm depending on the fetal stage of development and the magnitude of the radiation dose.

8.2 Lactation

Risk Summary

PYLARIFY is not indicated for use in females. There is no information on the presence of piflufolastat F 18 in human milk, the effect on the breastfed infant, or the effect on milk production.

8.4 Pediatric Use

The safety and effectiveness of PYLARIFY in pediatric patients have not been established.

8.5 Geriatric Use

Of the 593 patients in completed clinical studies of PYLARIFY, 355 (60%) were ≥65 years old, while 76 (12.8%) were ≥75 years old. The efficacy and safety of PYLARIFY appear similar in adult and geriatric patients with prostate cancer, although the number of patients in the trials was not large enough to allow definitive comparison.

10 OVERDOSAGE

In the event of an overdose of PYLARIFY, reduce the radiation absorbed dose to the patient where possible by increasing the elimination of the drug from the body using hydration and frequent bladder voiding. A diuretic might also be considered. If possible, an estimate of the radiation effective dose administered to the patient should be made.

11 DESCRIPTION

11.1 Chemical Characteristics

PYLARIFY contains fluorine 18 (F 18), radiolabeled prostate-specific membrane antigen inhibitor imaging agent. Chemically piflufolastat F 18 is 2-(3-{1-carboxy-5-[(6-[18F]fluoro-pyridine-3-carbonyl)-amino]-pentyl}ureido)-pentanedioic acid. The molecular weight is 441.4 and the structural formula is:

The chiral purity of the unlabeled piflufolastat F 18 precursor is greater than 99% (S,S).

PYLARIFY is a sterile, non-pyrogenic, clear, colorless solution for intravenous injection. Each milliliter contains 37 to 2,960 MBq (1 to 80 mCi) piflufolastat F 18 with ≤0.01 µg/mCi of piflufolastat at calibration time and date, and ≤ 78.9 mg ethanol in 0.9% sodium chloride injection USP. The pH of the solution is 4.5 to 7.0.

PYLARIFY has a radiochemical purity of at least 95% up to 10 hours following end of synthesis, and specific activity of at least 1000 mCi/µmol at the time of administration.

11.2 Physical Characteristics

PYLARIFY is radiolabeled with fluorine 18 (F 18), a cyclotron produced radionuclide that decays by positron emission to stable oxygen 18 with a half-life of 109.8 minutes. The principal photons useful for diagnostic imaging are the coincident pair of 511 keV gamma photons, resulting from the interaction of the emitted positron with an electron (Table 3).

Table 3. Principal Radiation Produced from Decay of Fluorine 18
 | Radiation Energy (keV) | Abundance (%)
Positron | 249.8 | 96.9
Gamma | 511 | 193.5

11.3 External Radiation

The point source air-kerma coefficient for F 18 is 3.75 × 10^-17Gy m^2/(Bq s). The first half-value thickness of lead (Pb) for F 18 gamma rays is approximately 6 mm. The relative reduction of radiation emitted by F 18 that results from various thicknesses of lead shielding is shown in Table 4. The use of 8 cm Pb decreases the radiation transmission (i.e. exposure) by a factor of about 10,000.

Table 4. Radiation Attenuation of 511 keV Gamma Rays by Lead Shielding
Shield Thickness cm of Lead (Pb) | Coefficient of Attenuation
0.6 | 0.5
2 | 0.1
4 | 0.01
6 | 0.001
8 | 0.0001

12 CLINICAL PHARMACOLOGY

12.1 Mechanism of Action

Piflufolastat F 18 binds to cells that express PSMA, including malignant prostate cancer cells, which usually overexpress PSMA. Fluorine-18 (F 18) is a β+ emitting radionuclide that enables positron emission tomography.

12.2 Pharmacodynamics

The relationship between piflufolastat F 18 plasma concentrations and image interpretation has not been studied.

12.3 Pharmacokinetics

Distribution

Following intravenous administration of piflufolastat F 18, blood levels decline in a biphasic fashion. The distribution half-life is 0.17 ± 0.044 hours and the elimination half-life is 3.47 ± 0.49 hours.

Piflufolastat F 18 distributes to the kidneys (16.5% of administered activity), liver (9.3%), and lung (2.9%), within 60 minutes of intravenous administration.

Elimination

Elimination is by urinary excretion. In the first 8 hours post-injection, approximately 50% of administered radioactivity is excreted in the urine.

13 NONCLINICAL TOXICOLOGY

13.1 Carcinogenesis, Mutagenesis, Impairment of Fertility

Animal studies to assess the carcinogenicity or mutagenic potential of piflufolastat have not been conducted. However, piflufolastat has the potential to be mutagenic because of the F 18 radioisotope.

No animal studies with piflufolastat have been performed to evaluate the potential impairment of fertility in males or females.

14 CLINICAL STUDIES

The safety and efficacy of PYLARIFY were evaluated in two prospective, open-label, multi-center clinical studies in men with prostate cancer: OSPREY (NCT02981368) and CONDOR (NCT03739684).

OSPREY

OSPREY enrolled a cohort of 268 men with biopsy-proven prostate cancer who were considered candidates for radical prostatectomy and pelvic lymph node dissection. These patients were all considered to have high risk disease based on criteria such as Gleason score, PSA level, and tumor stage. Each patient received a single PYLARIFY PET/CT from mid-thigh to skull vertex.

Three central readers independently interpreted each PET scan for the presence of abnormal PYLARIFY uptake in pelvic lymph nodes in multiple subregions, including the common iliac lymph nodes. The readers were blinded to all clinical information. While readers also recorded the presence of PYLARIFY PET-positive lesions in the prostate gland and outside the pelvis, those results were not included in the primary efficacy analysis.

A total of 252 patients (94%) underwent standard-of-care prostatectomy and template pelvic lymph node dissection and had sufficient histopathology data for evaluation of the pelvic lymph nodes. Surgical specimens were separated into three regions: left hemipelvis, right hemipelvis, and other. For each patient, PYLARIFY PET results and histopathology results obtained from dissected pelvic lymph nodes were compared by surgical region. PET results in locations that were not dissected were excluded from analysis.

For the 252 evaluable patients, the mean age was 64 years (range 46 to 84 years), and 87% were white. The median serum PSA was 9.3 ng/mL. The total Gleason score was 7 for 19%, 8 for 46%, and 9 for 34% of the patients, with the remainder of the patients having Gleason scores of 6 or 10.

Table 5 shows PYLARIFY PET performance by reader through comparison to pelvic lymph node histopathology at the patient-level with region matching, such that at least one true positive region defines a true positive patient. Approximately 24% of the evaluable patients had pelvic lymph node metastases based on histopathology (95% confidence interval: 19%, 29%).

Table 5: Patient-Level, Region-Matched Performance of PYLARIFY PET for Detection of Pelvic Lymph Node Metastasis in OSPREY (n=252)
 | Reader 1 | Reader 2 | Reader 3
True Positive | 23 | 17 | 23
False Positive | 7 | 4 | 9
False Negative | 36 | 43 | 37
True Negative | 186 | 188 | 183
Sensitivity, % (95% CI) | 39 (27, 51) | 28 (17, 40) | 38 (26, 51)
Specificity, % (95% CI) | 96 (94, 99) | 98 (95, 99) | 95 (92, 98)
PPV, % (95% CI) | 77 (62, 92) | 81 (59, 93) | 72 (56, 87)
NPV, % (95% CI) | 84 (79, 89) | 81 (76, 86) | 83 (78, 88)
Abbreviations: CI = confidence interval, PPV = positive predictive value, NPV = negative predictive value

In exploratory analyses, there were numerical trends towards more true positive results among patients with total Gleason score of 8 or higher and among patients with tumor stage of T2c or higher relative to those patients with lower Gleason score or tumor stage.

CONDOR

CONDOR enrolled 208 patients with biochemical evidence of recurrent prostate cancer, defined by serum PSA of at least 0.2 ng/mL after radical prostatectomy (with confirmatory PSA level also at least

0.2 ng/mL) or by an increase in serum PSA of at least 2 ng/mL above the nadir after other therapies. The mean age was 68 years (range 43 to 91 years), and 90% of patients were white. The median serum PSA was 0.82 ng/mL. Prior treatment included radical prostatectomy in 85% of the patients.

All enrolled patients had conventional imaging evaluation (for most patients, CT or MRI) within 60 days prior to receiving PYLARIFY PET, and this evaluation was negative or equivocal for prostate cancer. All patients received a single PYLARIFY PET/CT from mid-thigh to skull vertex with optional imaging of the lower extremities.

Three central readers independently evaluated each PYLARIFY PET scan for the presence and location of positive lesions. Location of each lesion was categorized in one of 19 subregions that were grouped into 5 regions (prostate/prostate bed, pelvic lymph nodes, other lymph nodes, soft tissue, bone). The readers were blinded to all clinical information.

Depending on the reader, a total of 123 to 137 patients (59% to 66%) had at least one lesion that was identified as PYLARIFY PET-positive (Table 6, TP + FP + PET-Positive Without Reference Standard). The region most commonly observed to have a PYLARIFY PET-positive finding was pelvic lymph nodes (40% to 42% of all PET-positive regions) and the least common region was soft tissue (6% to 7%).

Depending on the reader, 99 to 104 patients with a PYLARIFY PET-positive region had location-matched composite reference standard information available (Evaluable Set, Table 6, TP + FP) that consisted of histopathology, imaging (CT, MRI, ultrasound, fluciclovine PET, choline PET, or bone scan) obtained within 60 days of the PYLARIFY PET scan, or response of serum PSA level to targeted radiotherapy. Reference standard information for PET-negative regions was not systematically collected in this study.

Table 6 shows patient-level performance results of PYLARIFY PET by reader, including location -matched positive predictive value [true positive / (true positive + false positive)], also known as Correct Localization Rate (CLR). For these results, a patient was considered true positive if they had at least one matching location positive on both PYLARIFY PET and the composite reference standard. In addition to calculating location-matched positive predictive value in the Evaluable Set (CLR), an exploratory analysis of positive predictive value in all scanned patients (Imputed CLR) was performed in which PYLARIFY PET-positive patients who lacked reference standard information were imputed using an estimated likelihood that at least one PET-positive lesion was reference standard positive, based on patient-specific factors.

Table 6: Patient-Level Performance of PYLARIFY PET in CONDOR (n=208)
 | Reader 1 | Reader 2 | Reader 3
True Positive (TP) | 89 | 87 | 84
False Positive (FP) | 15 | 13 | 15
PET-Positive Without Reference Standard | 33 | 24 | 24
PET-Negative | 71 | 84 | 85
CLR % (95% CI) | 86 (79, 92) | 87 (80, 94) | 85 (78, 92)
Imputed CLR % (95% CI) | 78 (71, 85) | 81 (74, 88) | 79 (72, 86)
Abbreviations: TP = true positive, FP = false positive, CLR = location-matched positive predictive value in the Evaluable Set [TP/(TP + FP)], Imputed CLR = location-matched positive predictive value in all scanned patients using an imputation approach based on patient-specific factors for PET-Positive Without Reference Standard, CI = confidence interval

An exploratory analysis of region-level positive predictive value using only PET-positive regions that had sufficient composite reference standard information to determine true positive or false positive status demonstrated results of 67% to 70% with the lower bound of the 95% confidence interval ranging from 59% to 63%.

The percentage of patients categorized as true positive in a location-matched analysis out of all patients scanned with PYLARIFY was an additional exploratory endpoint. Using the same imputation approach for PET-positive patients who lacked reference standard information as in Table 6 above, this value was 47% to 51%, with the lower bound of the 95% confidence interval ranging from 40% to 45%.

Table 7 shows patient-level PYLARIFY PET results from the majority read stratified by serum PSA level. Percent PET positivity was calculated as the proportion of patients with a positive PYLARIFY PET out of all patients scanned. Percent PET positivity includes patients determined to be either true positive or false positive as well as those in whom such determination was not made due to lack of composite reference standard information. The likelihood of a patient having at least one PYLARIFY PET-positive lesion generally increased with higher serum PSA level.

Table 7: Patient-Level PYLARIFY PET Results and Percent PET Positivity [Percent PET positivity = PET positive patients/total patients scanned. PET positive patients include true positive and false positive patients as well as those who did not have reference standard information.] Stratified by Serum PSA Level in the CONDOR Study Using Majority Result Among Three Readers (n=199) [Six patients were excluded from this table due to lack of baseline PSA level. Three patients were excluded from this table due to lack of majority result among the categories true positive, false positive, PET positive without reference standard, and PET negative.]
PSA (ng/mL) | PET positive patients |  |  |  | PET negative patients | Percent PET positivity, (95% CI)
PSA (ng/mL) | Total | TP | FP | Without reference standard | PET negative patients | Percent PET positivity, (95% CI)
PSA (ng/mL) | Total | With reference standard |  | Without reference standard | PET negative patients | Percent PET positivity, (95% CI)
<0.5 | 24 | 11 | 4 | 9 | 45 | 35 (24, 46)
<0.5 | 24 | 15 |  | 9 | 45 | 35 (24, 46)
≥0.5 and <1 | 18 | 12 | 3 | 3 | 18 | 50 (34, 66)
≥0.5 and <1 | 18 | 15 |  | 3 | 18 | 50 (34, 66)
≥1 and <2 | 21 | 15 | 3 | 3 | 10 | 68 (51, 84)
≥1 and <2 | 21 | 18 |  | 3 | 10 | 68 (51, 84)
≥2 | 57 | 50 | 3 | 4 | 6 | 90 (83, 98)
≥2 | 57 | 53 |  | 4 | 6 | 90 (83, 98)
Total | 120 | 88 | 13 | 19 | 79 | 60 (54, 67)
Total | 120 | 101 |  | 19 | 79 | 60 (54, 67)
Abbreviations: TP = true positive, FP = false positive, CI = confidence interval

16 HOW SUPPLIED/STORAGE AND HANDLING

16.1 How Supplied

PYLARIFY injection is supplied in a 50 mL multiple-dose glass vial (NDC# 71258-022-01) containing a clear, colorless solution at a strength of 37 MBq/mL to 2,960 MBq/mL (1 mCi/mL to 80 mCi/mL) piflufolastat F 18 at calibration time and date.

16.2 Storage and Handling

Storage

Store PYLARIFY at controlled room temperature (USP) 20°C to 25°C (68°F to 77°F). PYLARIFY does not contain a preservative. Store PYLARIFY in the original container with radiation shielding. The expiration date and time are provided on the container label. Use PYLARIFY within 10 hours from the time of end of synthesis.

Handling

This preparation is approved for use by persons under license by the Nuclear Regulatory Commission or the relevant regulatory authority of an Agreement State.

17 PATIENT COUNSELING INFORMATION

Adequate Hydration

Instruct patients to drink a sufficient amount of water to ensure adequate hydration before their PET study and urge them to drink and urinate as often as possible during the first hours following the administration of PYLARIFY, in order to reduce radiation exposure [ see Dosage and Administration (2.3)and Warnings and Precautions (5.3)].

Manufactured for:
Progenics Pharmaceuticals, Inc., a Lantheus company
331 Treble Cove Road
N. Billerica, MA 01862

PYLARIFY®is a trademark of Progenics Pharmaceuticals, Inc.

Patent: http://www.lantheus.com/patents/index.html

516091-0323

PRINCIPAL DISPLAY PANEL - 80 mCi/mL Vial Label

Sterile

PYLARIFY®
(piflufolastat F 18) injection

Non-pyrogenic

37 MBq/mL to 2,960 MBq/mL (1 mCi/mL to 80 mCi/mL)
at end of synthesis (EOS)
Diagnostic – For Intravenous Use Only
Expires within 10 hours from EOS

Batch #: _________

EOS Date:_________EOS Time: _________

Activity @ EOS:_________mCi

Concentration:_________mCi/mL

Volume:_________mL

Exp. Date:_________Exp. Time: _________